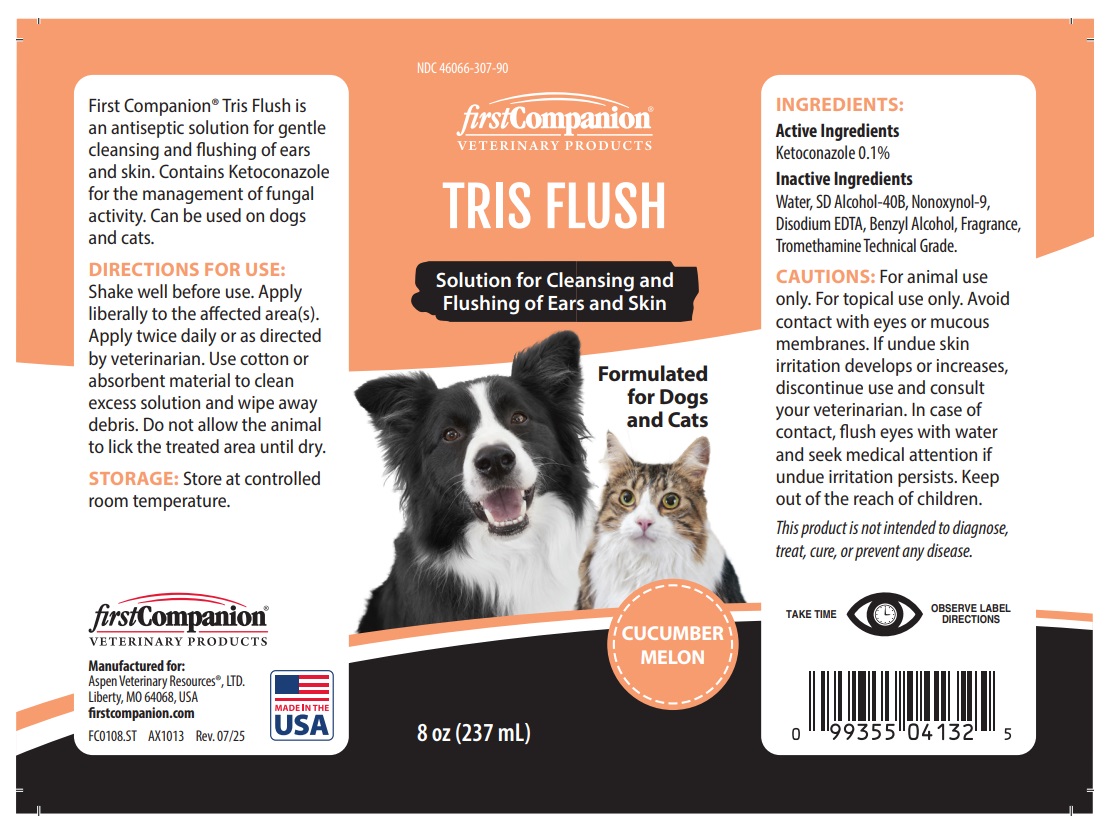 DRUG LABEL: firstCompanion TRIS FLUSH
NDC: 46066-307 | Form: SOLUTION
Manufacturer: Aspen Veterinary Resources, Ltd.
Category: animal | Type: OTC ANIMAL DRUG LABEL
Date: 20250925

ACTIVE INGREDIENTS: KETOCONAZOLE 0.1 g/100 mL
INACTIVE INGREDIENTS: WATER; ALCOHOL; NONOXYNOL-9; EDETATE DISODIUM; BENZYL ALCOHOL; TROMETHAMINE

firstCompanion® VETERINARY PRODUCTS TRIS FLUSH

Active Ingredients

Ketoconazole 0.1%

Inactive Ingredients

Water, SD Alcohol-40B, Nonoxynol-9, Disodium EDTA, Benzyl Alcohol, Fragrance, Tromethamine Technical Grade.

CAUTIONS:

For animal use only. For topical use only. Avoid contact with eyes or mucous membranes. If undue skin irritation develops or increases, discontinue use and consult your veterinarian. In case of contact, flush eyes with water and seek medical attention if undue irritation persists. Keep out of the reach of children.
This product is not intended to diagnose, treat, cure, or prevent any disease.

DIRECTIONS FOR USE:

Shake well before use. Apply liberally to the affected area(s). Apply twice daily or as directed by veterinarian. Use cotton or absorbent material to clean excess solution and wipe away debris. Do not allow the animal to lick the treated area until dry.

STORAGE:

Store at controlled room temperature.

Solution for Cleansing and Flushing of Ears and Skin

Formulated for Dogs and Cats

CUCUMBER
MELON

TAKE TIME

OBSERVE LABEL DIRECTIONS

First Companion® Tris Flush is an antiseptic solution for gentle cleansing and flushing of ears and skin. Contains Ketoconazole for the management of fungal activity. Can be used on dogs and cats.

Manufactured for:
Aspen Veterinary Resources®, LTD.
Liberty, MO 64068, USA

firstcompanion.com

MADE IN THE USA